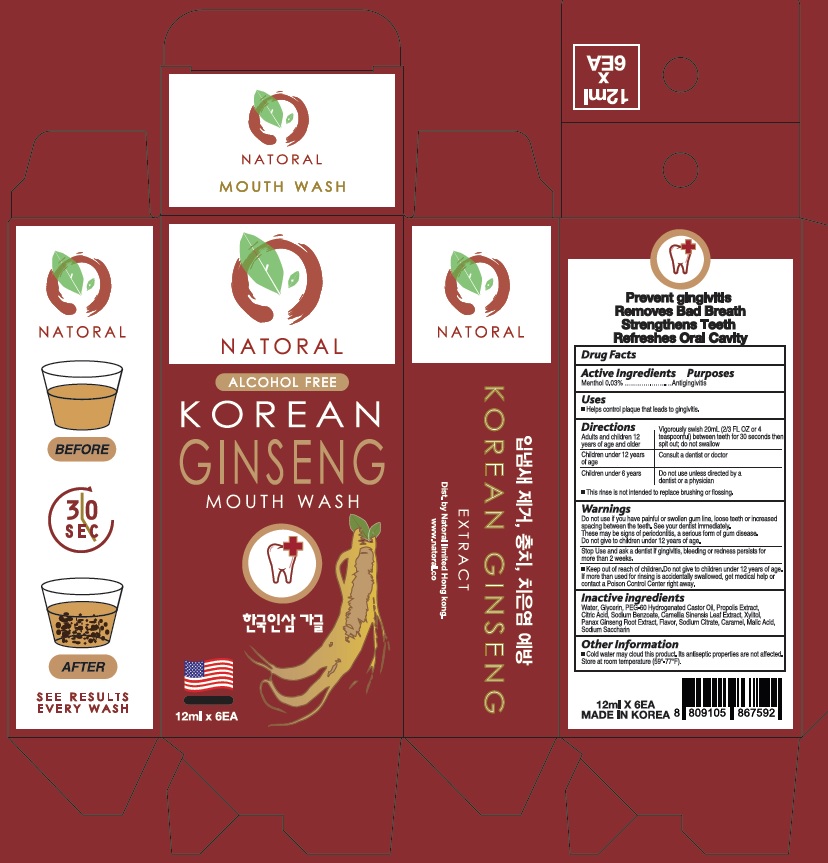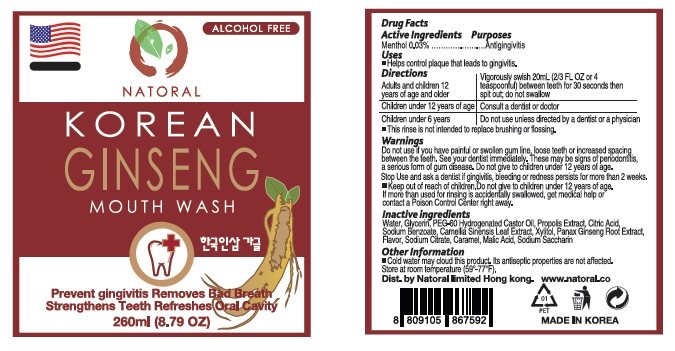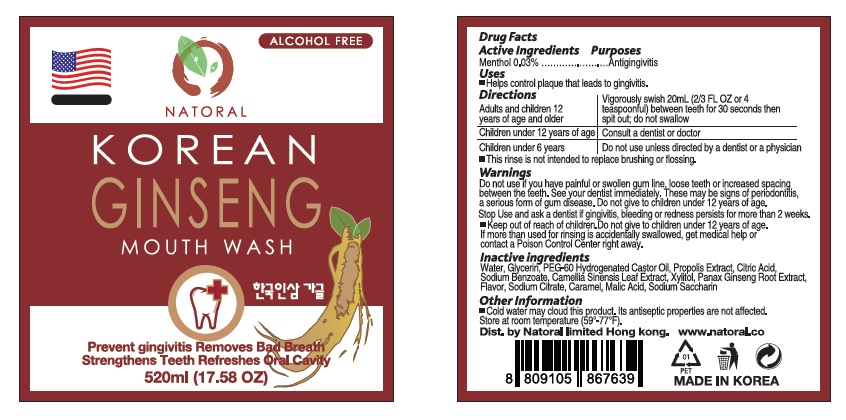 DRUG LABEL: Natoral Korean Ginseng
NDC: 71211-001 | Form: MOUTHWASH
Manufacturer: Natoral Limited
Category: otc | Type: HUMAN OTC DRUG LABEL
Date: 20170202

ACTIVE INGREDIENTS: MENTHOL, UNSPECIFIED FORM 0.3 mg/1 mL
INACTIVE INGREDIENTS: WATER; GLYCERIN; PEG-60 HYDROGENATED CASTOR OIL; PROPOLIS WAX; CITRIC ACID MONOHYDRATE; SODIUM BENZOATE; GREEN TEA LEAF; XYLITOL; ASIAN GINSENG; SODIUM CITRATE, UNSPECIFIED FORM; CARAMEL; MALIC ACID; SACCHARIN SODIUM

Drug Facts

ACTIVE INGREDIENT

Menthol 0.03%

PURPOSE

Antigingivitis

INDICATIONS AND USAGE

Helps control plaque that leads to gingivitis.

DOSAGE AND ADMINISTRATION

Adults and children 12 years of age and older Vigorously swish 20mL (2/3 FL OZ or 4 teaspoonful) between teeth for 30 seconds then spit out; do not swallow
Children under 12 years of age Consult a dentist or doctor
Children under 6 years Do not use unless directed by a dentist or a physician

- This rinse is not intended to replace brushing or flossing.

- Do not use if you have painful or swollen gum line, loose teeth or increased spacing between the teeth. See your dentist immediately. These may be signs of periodontitis, a serious form of gum disease. Do not give to children under 12 years of age.

- Stop Use and ask a dentist if gingivitis, bleeding or redness persists for more than 2 weeks.

KEEP OUT OF REACH OF CHILDREN

Do not give to children under 12 years of age. If more than used for rinsing is accidentally swallowed, get medical help or contact a Poison Control Center right away.

INACTIVE INGREDIENT

Water, Glycerin, PEG-60 Hydrogenated Castor Oil, Propolis Extract, Citric Acid, Sodium Benzoate, Camellia Sinensis Leaf Extract, Xylitol, Panax Ginseng Root Extract, Flavor, Sodium Citrate, Caramel, Malic Acid, Sodium Saccharin

PACKAGE LABEL

12 mL Sachet x 6

PACKAGE LABEL

260 mL Bottle

PACKAGE LABEL

520 mL Bottle